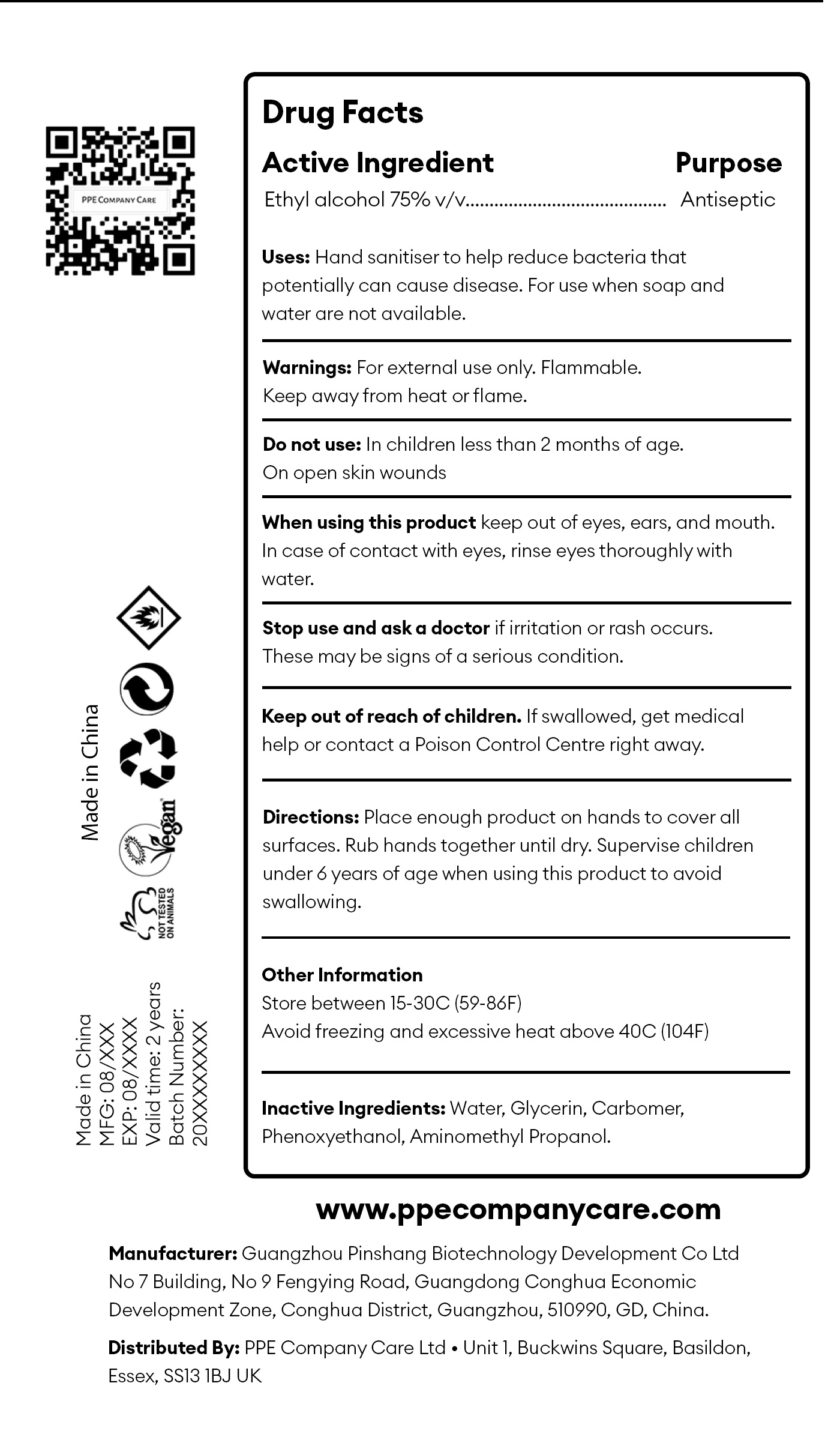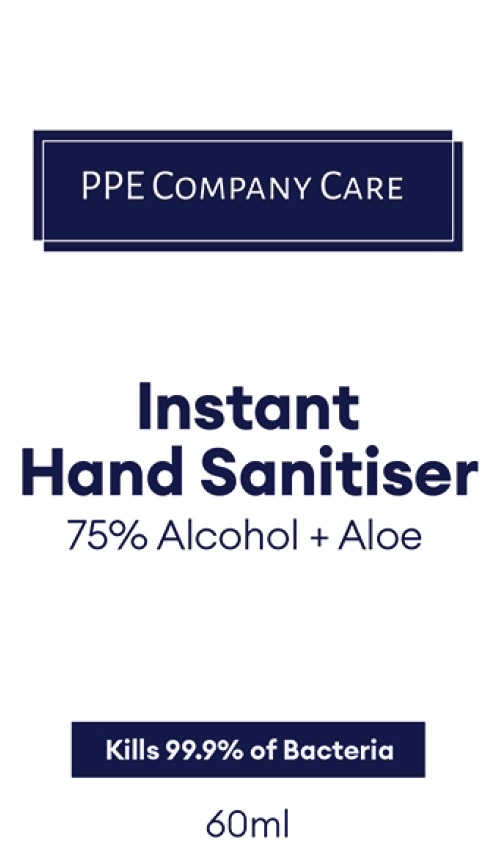 DRUG LABEL: PPE Company Care Instant Hand Sanitiser
NDC: 80856-000 | Form: GEL
Manufacturer: PPE Company Care Ltd
Category: otc | Type: HUMAN OTC DRUG LABEL
Date: 20201109

ACTIVE INGREDIENTS: ALCOHOL 0.75 mL/1 mL
INACTIVE INGREDIENTS: WATER; GLYCERIN; CARBOMER HOMOPOLYMER, UNSPECIFIED TYPE; PHENOXYETHANOL; AMINOMETHYLPROPANOL

PPE Company Care Instant Hand Sanitiser

Active Ingredient

Ethyl alcohol 75% v/

Purpose

Antiseptic

Uses:

Hand sanitiser to help reduce bacteria that potentially can cause disease. For use when soap and water are not available.

Warnings:

For external use only. Flammable.

Keep away from heat or flame.

Do not use

In children less than 2 months of age.
On open skin wounds

When using this product

keep out of eyes, ears, and mouth. In case of contact with eyes, rinse eyes thoroughly with water.

Stop use and ask a doctor

if irritation or rash occurs. These may be signs of a serious condition.

Keep out of reach of children.

If swallowed, get medical help or contact a Poison Control Centre right away.

Directions:

Place enough product on hands to cover all surfaces. Rub hands together until dry. Supervise children under 6 years of age when using this product to avoid swallowing.

Other Information

Store between 15-30C (59-86F)
Avoid freezing and excessive heat above 40C (104F)

Inactive Ingredients:

Water, Glycerin, Carbomer, Phenoxyethanol, Aminomethyl Propanol.